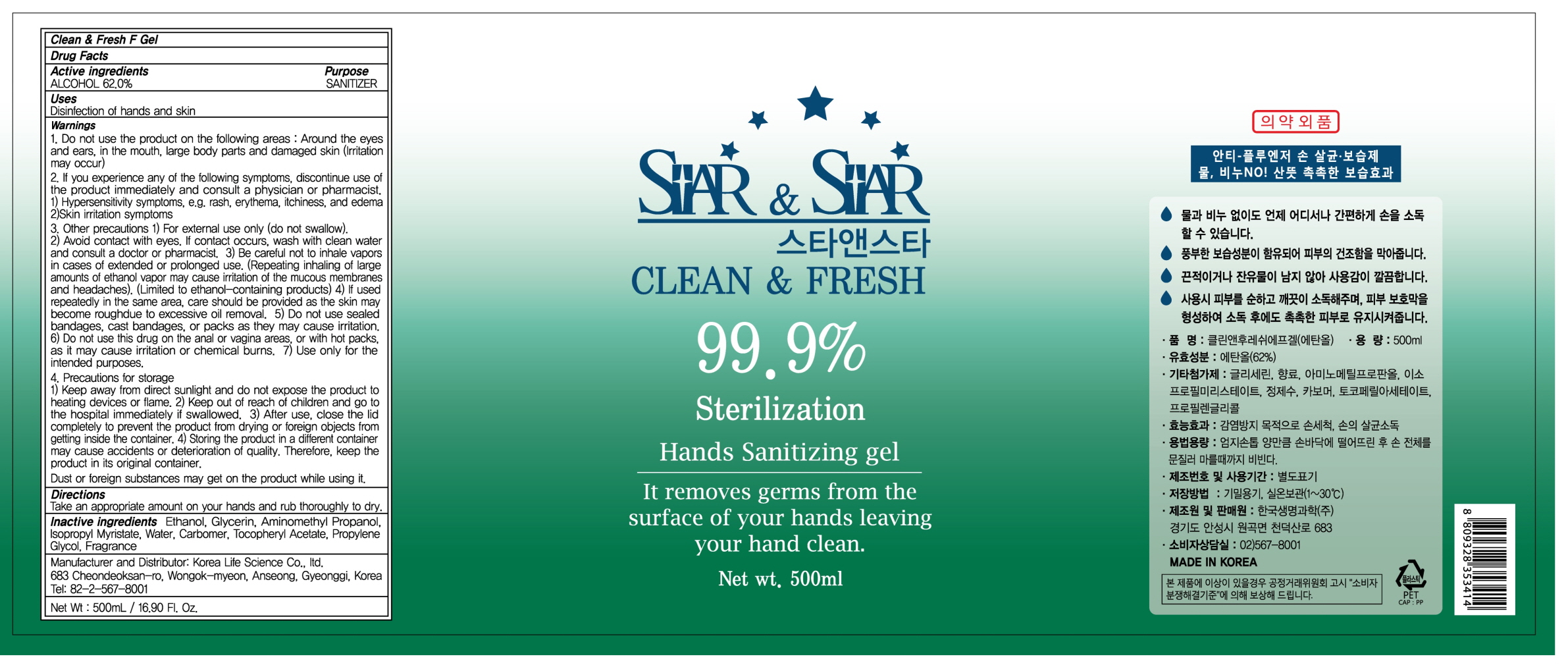 DRUG LABEL: Clean And Fresh F
NDC: 74406-130 | Form: GEL
Manufacturer: Korea Life Science Co.,ltd
Category: otc | Type: HUMAN OTC DRUG LABEL
Date: 20200615

ACTIVE INGREDIENTS: ALCOHOL 310 mL/500 mL
INACTIVE INGREDIENTS: Glycerin; AminomethylPropanol; Isopropyl Myristate; Water; CARBOMER HOMOPOLYMER, UNSPECIFIED TYPE; .ALPHA.-TOCOPHEROL ACETATE; Propylene Glycol

ACTIVE INGREDIENT

ALCOHOL 62.0%

INACTIVE INGREDIENT

Glycerin, Aminomethyl Propanol, Isopropyl Myristate, Water, Carbomer, Tocopheryl Acetate, Propylene Glycol, Fragrance

PURPOSE

SANITIZER

WARNINGS

1.Do not use the product on the following areas:

Around the eyes and ears, in the mouth, large body parts and damaged skin(Irritation may occur)

2.If you experience any of the following symptoms, discontinue use of the product immediately and consult a physician or pharmacist.
1) Hypersensitivity symptoms, e.g. rash, erythema, itchiness, and edema
2)Skin irritation symptoms

3.Other precautions
1) For external use only (do not swallow).
2) Avoid contact with eyes. If contact occurs, wash with clean water and consult a doctor or pharmacist.
3)Be careful not to inhale vapors in cases of extended or prolonged use. (Repeating inhaling of large amounts of ethanol vapor may cause irritation of the mucous membranes and headaches).
(Limited to ethanol-containing products)
4) If used repeatedly in the same area, care should be provided as the skin may become rough due to excessive oil removal.
5) Do not use sealed bandages, cast bandages, or packs as they may cause irritation.
6) Do not use this drug on the anal or vagina areas, or with hot packs, as it may cause irritation or chemical burns.
7) Use only for the intended purposes.

4.Precautions for storage
1) Keep away from direct sunlight and do not expose the product to heating devices or flame.
2) Keep out of reach of children and go to the hospital immediately if swallowed.
3) After use, close the lid completely to prevent the product from drying or foreign objects from getting inside the container.
4) Storing the product in a different container may cause accidents or deterioration of quality. Therefore, keep the product in its original container.

Dust or foreign substances may get on the product while using it.

Keep out of reach of children and go to the hospital immediately if swallowed.

Uses

Disinfection of hands and skin

Directions

Take an appropriate amount on your hands and rub thoroughly to dry.